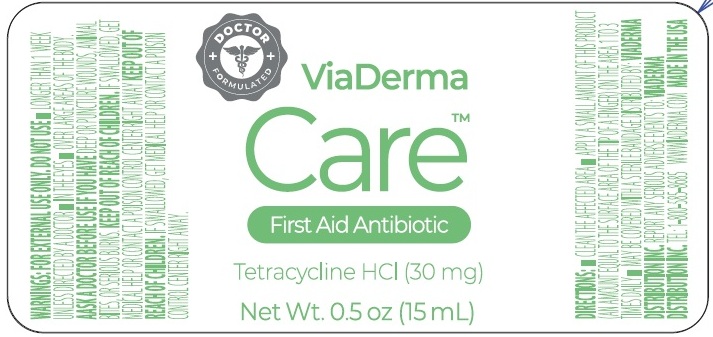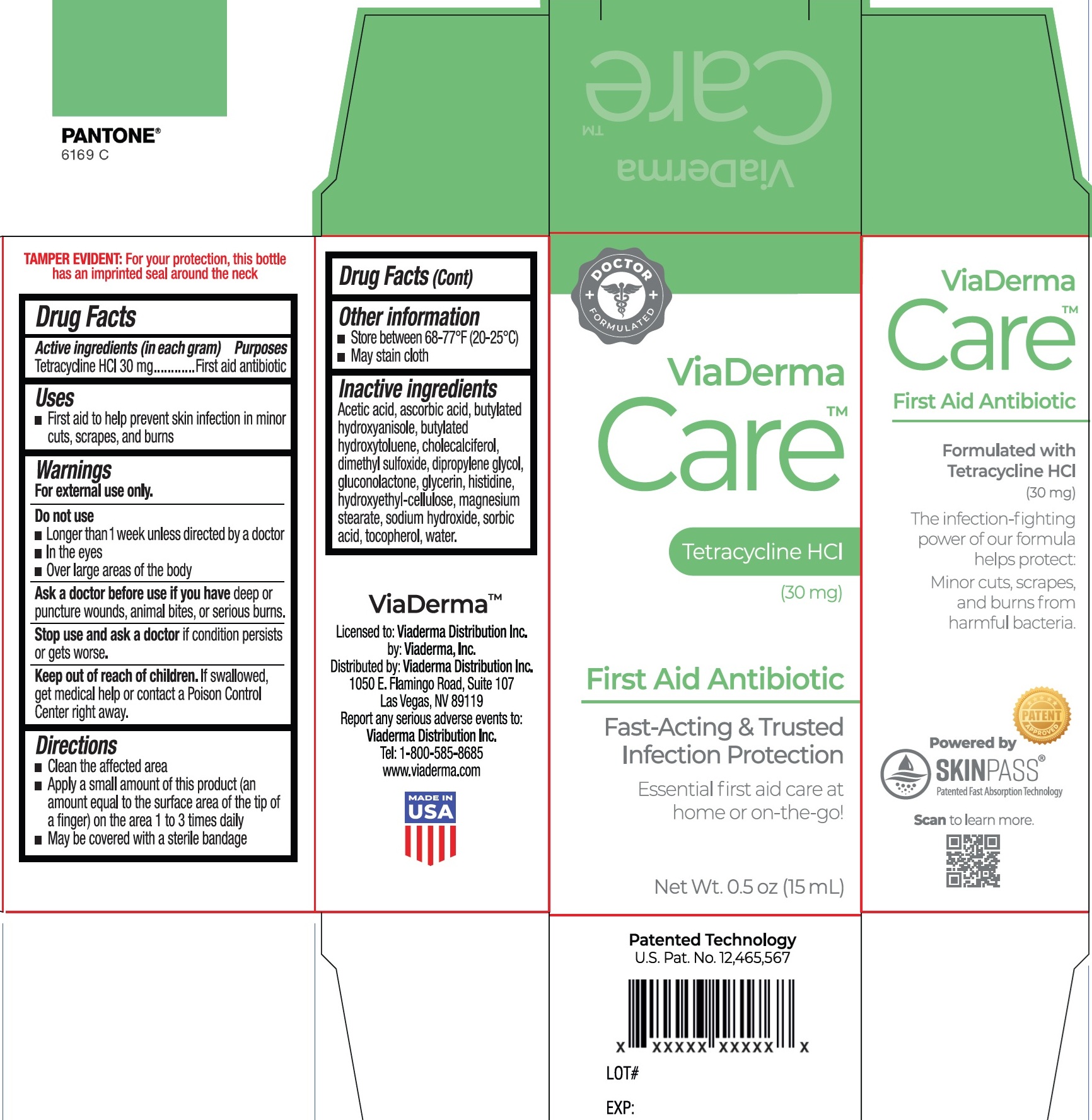 DRUG LABEL: ViaDerma Care Tetracycline HCl First Aid Antibiotic
NDC: 71262-021 | Form: SOLUTION
Manufacturer: ViaDerma Distribution, Inc.
Category: otc | Type: HUMAN OTC DRUG LABEL
Date: 20260114

ACTIVE INGREDIENTS: TETRACYCLINE HYDROCHLORIDE 30 mg/1 mL
INACTIVE INGREDIENTS: ACETIC ACID; ASCORBIC ACID; BUTYLATED HYDROXYANISOLE; BUTYLATED HYDROXYTOLUENE; CHOLECALCIFEROL; DIMETHYL SULFOXIDE; DIPROPYLENE GLYCOL; GLUCONOLACTONE; GLYCERIN; HISTIDINE; HYDROXYETHYL CELLULOSE, UNSPECIFIED; MAGNESIUM STEARATE; SODIUM HYDROXIDE; SORBIC ACID; TOCOPHEROL; WATER

ViaDerma Care Tetracycline HCl First Aid Antibiotic

Active ingredients (in each gram)

Tetracycline HCl 30 mg

Purposes

First aid antibiotic

Uses

- First aid to help prevent skin infection in minor cuts, scrapes, and burns

Warnings

For external use only.

Do not use

- Longer than 1 week unless directed by a doctor
- In the eyes
- Over large areas of the body

Ask a doctor before use if you have

deep or puncture wounds, animal bites, or serious burns.

Stop use and ask a doctor if

condition persists or gets worse.

Keep out of reach of children.

If swallowed, get medical help or contact a Poison Control Center right away.

Directions

- Clean the affected area
- Apply a small amount of this product (an amount equal to the surface area of the tip of a finger) on the area 1 to 3 times daily
- May be covered with a sterile bandage

Other information

• Store between 68°-77°F (20-25°C)
• May stain cloth

Inactive ingredients

Acetic acid, ascorbic acid, butylated hydroxyanisole, butylated hydroxytoluene, cholecalciferol, dimethyl sulfoxide, dipropylene glycol, gluconolactone, glycerin, histidine, hydroxyethyl-cellulose, magnesium stearate, sodium hydroxide, sorbic acid, tocopherol, water.